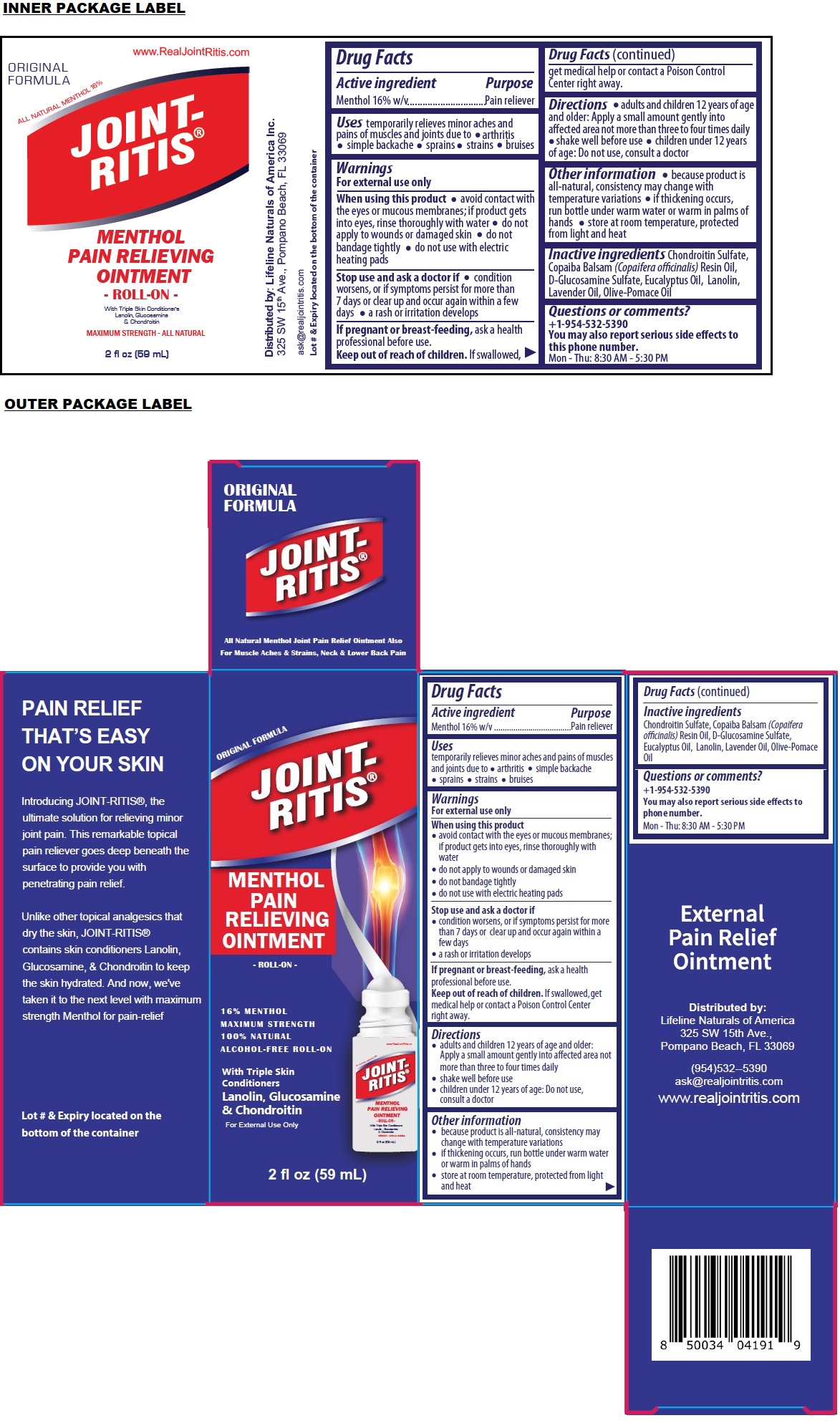 DRUG LABEL: JOINT-RITIS PAIN RELIEVING ROLL-ON
NDC: 83623-161 | Form: OINTMENT
Manufacturer: Lifeline Naturals of America, Inc.
Category: otc | Type: HUMAN OTC DRUG LABEL
Date: 20241030

ACTIVE INGREDIENTS: MENTHOL, UNSPECIFIED FORM 16 g/100 mL
INACTIVE INGREDIENTS: CHONDROITIN SULFATE (BOVINE); COPAIBA OIL; GLUCOSAMINE SULFATE; EUCALYPTUS OIL; LANOLIN; LAVENDER OIL; OLIVE OIL

JOINT-RITIS® MENTHOL PAIN RELIEVING OINTMENT

Active ingredient

Menthol 16% w/v

Purpose

Pain reliever

Uses

temporarily relieves minor aches and pains of muscles and joints due to arthritis • simple backache • sprains • strains • bruises

Warnings

For external use only

When using this product
• avoid contact with the eyes or mucous membranes; if product gets into eyes, rinse thoroughly with water
• do not apply to wounds or damaged skin
• do not bandage tightly
• do not use with electric heating pads

Stop use and ask a doctor if
• condition worsens, or if symptoms persist for more than 7 days or clear up and occur again within a few days
• a rash or irritation develops

If pregnant or breast-feeding, ask a health professional before use.

Keep out of reach of children. If swallowed, get medical help or contact a Poison Control Center right away.

Directions

• adults and children 12 years of age and older: Apply a small amount gently into affected area not more than three to four times daily
• shake well before use
• children under 12 years of age: Do not use, consult a doctor

Other information

• because product is all-natural, consistency may change with temperature variations
• if thickening occurs, run bottle under warm water or warm in palms of hands
• store at room temperature, protected from light and heat

Inactive ingredients

Chondroitin Sulfate, Copaiba Balsam (Copaifera officinalis) Resin Oil, D-Glucosamine Sulfate, Eucalyptus Oil, Lanolin, Lavender Oil, Olive-Pomace Oil

Questions or comments?

+1-954-532-5390
You may also report serious side effects to phone number.
Mon - Thu: 8:30 AM - 5:30 PM

ORIGINAL FORMULA

MAXIMUM STRENGTH
100% NATURAL
ALCOHOL-FREE ROLL-ON

Distributed by:
Lifeline Naturals of America
325 SW 15th Ave.,
Pompano Beach, FL 33069
(954)532--5390
ask@realjointritis.com
www.realjointritis.com

PAIN RELIEF THAT’S EASY ON YOUR SKIN

Introducing JOINT-RITIS®, the ultimate solution for relieving minor joint pain. This remarkable topical pain reliever goes deep beneath the surface to provide you with penetrating pain relief.

Unlike other topical analgesics that dry the skin, JOINT-RITIS® contains skin conditioners Lanolin, Glucosamine, & Chondroitin to keep the skin hydrated. And now, we've taken it to the next level with maximum strength Menthol for pain-relief

Lot # & Expiry located on the bottom of the container

All Natural Menthol Joint Pain Relief Ointment Also For Muscle Aches & Strains, Neck & Lower Back Pain